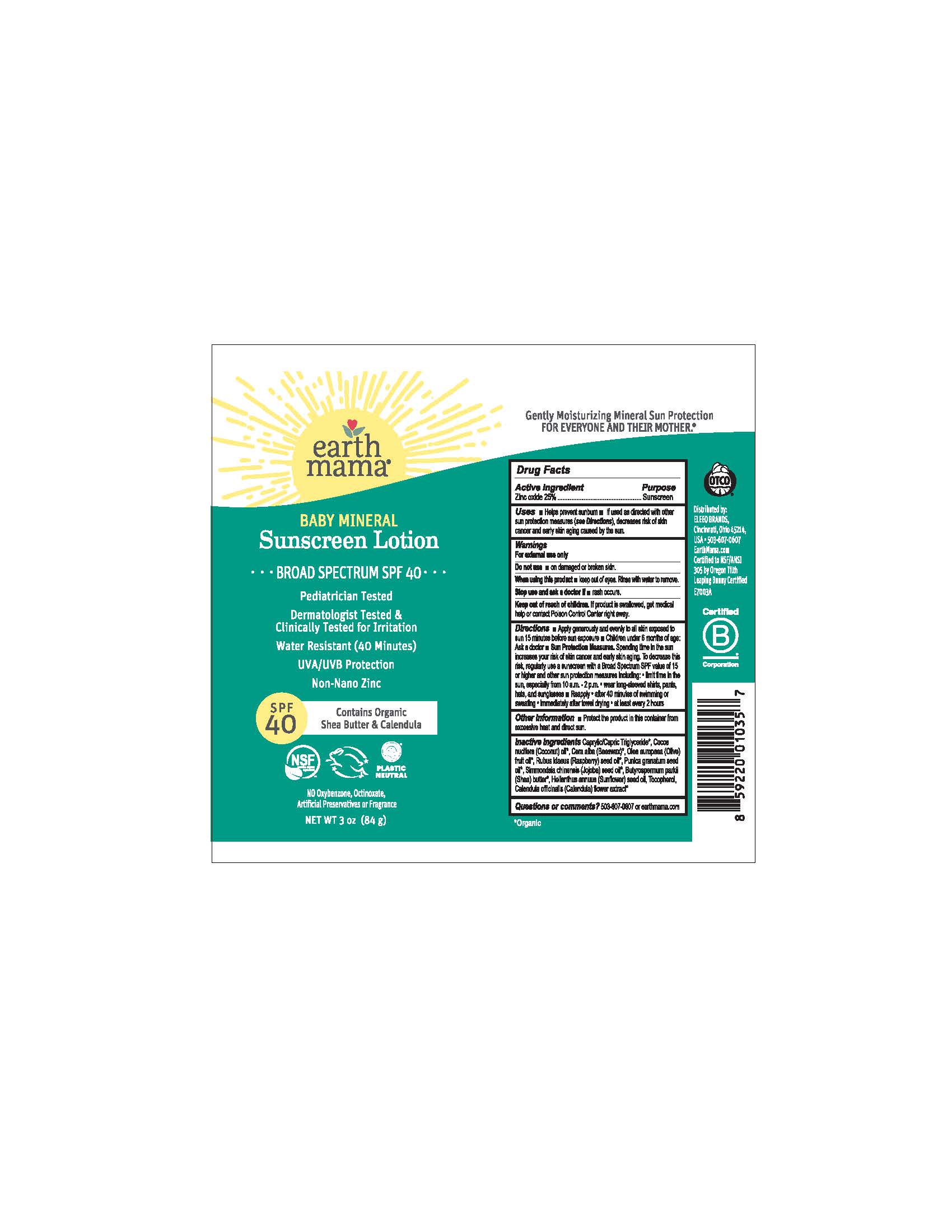 DRUG LABEL: Earth Mama Baby Mineral Sunscreen SPF 40
NDC: 79747-144 | Form: CREAM
Manufacturer: Eleeo Brands LLC
Category: otc | Type: HUMAN OTC DRUG LABEL
Date: 20250813

ACTIVE INGREDIENTS: ZINC OXIDE 250 mg/1 g
INACTIVE INGREDIENTS: COCONUT OIL; MEDIUM-CHAIN TRIGLYCERIDES; YELLOW WAX; OLIVE OIL; RUBUS IDAEUS SEED; POMEGRANATE SEED OIL; JOJOBA OIL; SHEA BUTTER; TOCOPHEROL; CALENDULA OFFICINALIS FLOWER

Earth Mama Baby Mineral Sunscreen SPF 40

Active Ingredient

Zinc Oxide 25%

Purpose

Sunscreen

Uses

• Helps prevent sunburn • If used as directed with other sun protection measures (see Directions), decreases risk of skin cancer and early skin aging caused by the sun.

Warnings

For external use only

Do not use • on damaged or broken skin.

When using this product • keep out of eyes. Rinse with water to remove.

Stop use and ask a doctor if • rash occurs

Keep out of reach of children. If product is swallowed, get medical help or contact Poison Control Center right away.

Directions

• Apply generously and evenly to all skin exposed to sun 15 minutes before sun exposure • Children under 6 months of age: Ask a doctor • Sun Protection Measures. Spending time in the sun increases your risk of skin cancer and early skin aging. To decrease this risk, regularly use a sunscreen with a Broad Spectrum SPF value of 15 or higher and other sun protection measures including: • limit time in the sun, especially from 10 a.m. - 2 p.m. • wear long-sleeved shirts, pants, hats, and sunglasses • Reapply • after 40 minutes of swimming or sweating • immediately after towel drying • at least every 2 hours

Other Information

• Protect the product in this container from excessive heat and direct sun.

Inactive Ingredients

Cocos Nucifera (Coconut) Oil*, Cocos Nucifera (Fractionated Coconut) Oil*, Cera Alba (Beeswax)*, Olea Europaea (Olive) Fruit Oil*, Rubus Idaeus (Red Raspberry) Seed Oil*, Punica Granatum (Pomegranate) Seed Oil*, Simmondsia Chinensis (Jojoba) Seed Oil*,Butyrospermum Parkii (Shea) Butter*, Tocopherol, Calendula Officinalis (Calendula) Flower Extract*

*Organic

Questions or comments?

503-607-0607 or earthmama.com

BROAD SPECTRUM SPF 40

Pediatrician Tested

Dermatologist Tested & Clinically Tested for Irritation

Water Resistant (40 Minutes)

UVA/UVB Protection

Non-Nano / Reef-Friendly

Contains Organic Shea Butter & Calendula

NSF
contains organic ingredients

PLASTIC NEUTRAL

NO Oxybenzone, Octinoxate, Artificial Preservatives or Fragrance

Gently Moisturizing Mineral Sun Protection
FOR EVERYONE AND THEIR MOTHER.®

Distributed by
Earth Mama Angel Baby®LLC
9866 SE Empire Ct.
Clackamas, OR 97015 USA
Certified to NSF/ANSI 305 by Oregon Tilth
Leaping Bunny certified